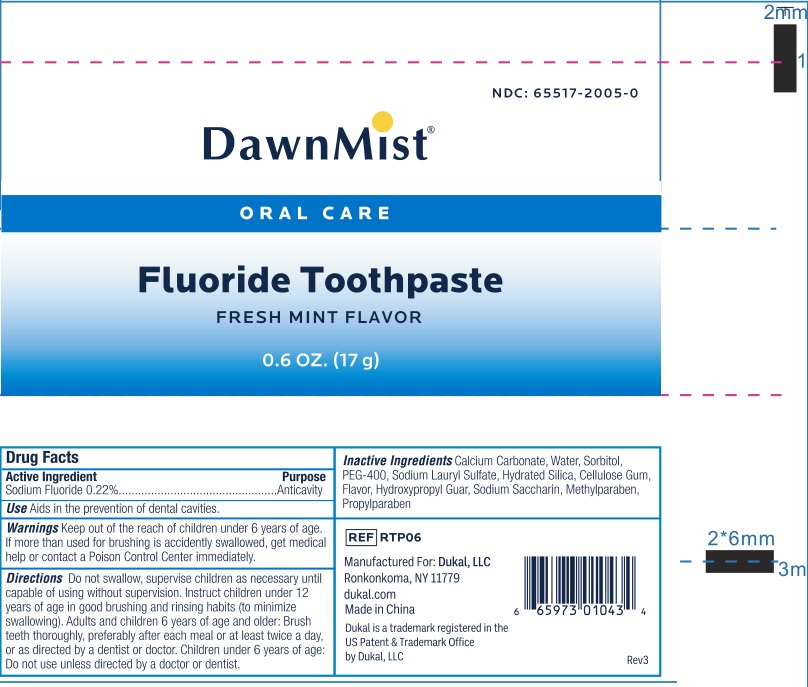 DRUG LABEL: DawnMist Fluoride Tooth
NDC: 70766-015 | Form: PASTE, DENTIFRICE
Manufacturer: Yangzhou SION Commodity Co.,Ltd
Category: otc | Type: HUMAN OTC DRUG LABEL
Date: 20240429

ACTIVE INGREDIENTS: SODIUM FLUORIDE 0.1 g/100 g
INACTIVE INGREDIENTS: WATER; SORBITOL; HYDRATED SILICA; SODIUM LAURYL SULFATE; METHYLPARABEN; PROPYLPARABEN; CALCIUM CARBONATE; HYDROXYPROPYL GUAR (2500-4500 MPA.S AT 1%); SACCHARIN SODIUM

70766-015 DawnMist

Active ingredients

SODIUM FLUORIDE 0.22%(0.10 w/v Fluoride ion)

<text xmlns="urn:hl7-org:v3"> <paragraph>SODIUM FLUORIDE 0.24%(0.11 w/v Fluoride ion)</paragraph> <paragraph/>&lt;text xmlns="urn:hl7-org:v3"> &lt;paragraph>SODIUM FLUORIDE 0.24%(0.11 w/v Fluoride ion)&lt;/paragraph> &lt;paragraph/>&amp;lt;text xmlns="urn:hl7-org:v3"> &amp;lt;paragraph>SODIUM FLUORIDE 0.24%(0.10 w/v Fluoride ion)&amp;lt;/paragraph> &amp;lt;paragraph/>&amp;amp;lt;text xmlns="urn:hl7-org:v3"> &amp;amp;lt;paragraph>SODIUM FLUORIDE 0.24%(0.10 w/v Fluoride ion)&amp;amp;lt;/paragraph> &amp;amp;lt;paragraph/>&amp;amp;amp;lt;text xmlns="urn:hl7-org:v3"> &amp;amp;amp;lt;paragraph>SODIUM FLUORIDE 0.24%(0.10 w/v Fluoride ion)&amp;amp;amp;lt;/paragraph> &amp;amp;amp;lt;paragraph/> &amp;amp;amp;lt;/text>&amp;amp;lt;/text>&amp;lt;/text>&lt;/text></text>

Purpose

Anticavity

Uses

Aids in the prevention of dental cavities.

Warnings

Keep out of the reach of children under 6 years of age. If you accidently swallow more than used for brushing, get medical help or contact a Poison Control Center immediately.

Keep out of reach of children.

Directions

- Do not swallow, supervise children as necessary until capable of using without supervision. Instruct children under 12 years of age in good brushing and rinsing habits (to minimizing swallowing).
- Adults and children 6 years of age and older: Brush teeth thoroughly, preferrably after each meal or at least twice a day, or as directed by a dentist or a doctor.
- Children under 6 years of age: Do not use unless directed by a doctor or dentist.

INACTIVE INGREDIENT

Calcium Carbonate, Water, Sorbitol, PEG-400, Sodium Lauryl Sulfate, Hydrated Silica, Cellulose Gum, Flavor, Hydroxypropyl Guar, , Sodium Sacharine, Methylparaben, Propylparaben